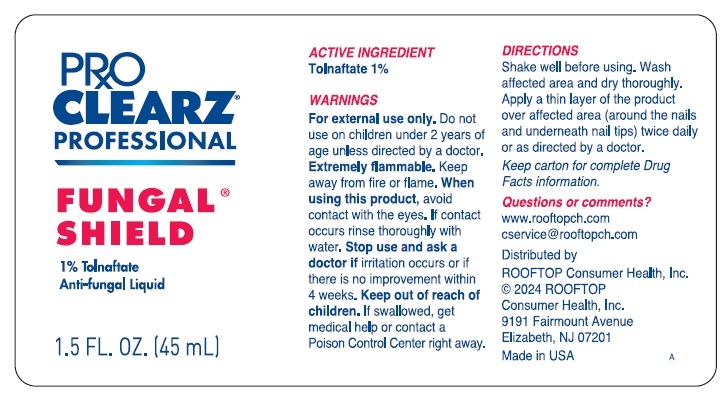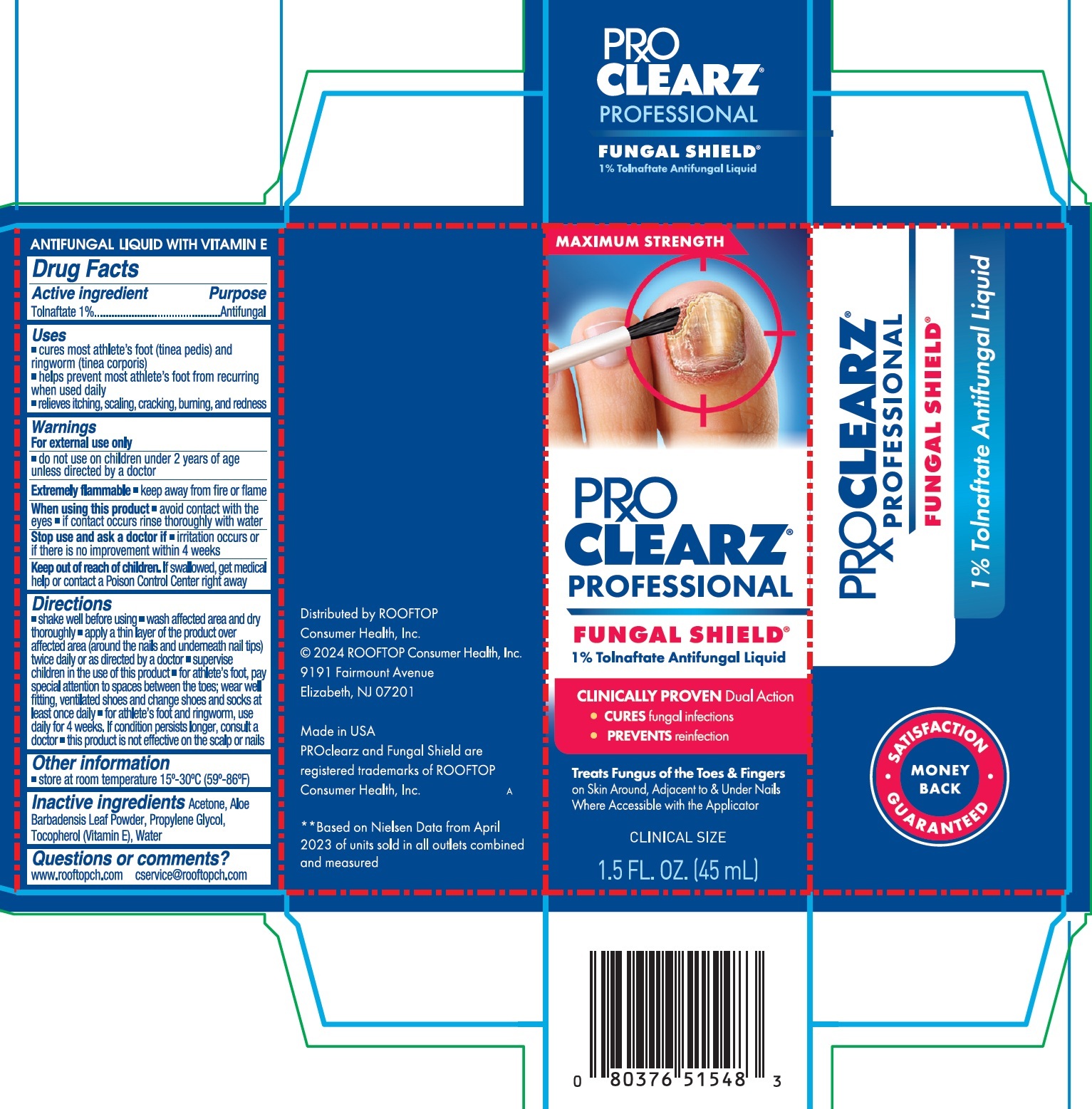 DRUG LABEL: Proclearz Professional Fungal Shield
NDC: 29784-184 | Form: LIQUID
Manufacturer: Rooftop Consumer health, inc
Category: otc | Type: HUMAN OTC DRUG LABEL
Date: 20260129

ACTIVE INGREDIENTS: TOLNAFTATE 10 mg/1 mL
INACTIVE INGREDIENTS: ACETONE; ALOE VERA LEAF; PROPYLENE GLYCOL; TOCOPHEROL; WATER

Proclearz Professional Fungal Shield

Active ingredient

Tolnaftate 1%

Purpose

Antifungal

Uses

- cures most athlete's foot (tinea pedis) and ringworm (tinea corporis)
- helps prevent most athlete's foot from recurring when used daily
- relieves itching, scaling, cracking, burning, and redness

Warnings

For external use only

- do not use on children under 2 years of age unless directed by a doctor

Extremely flammable• keep away from fire or flame

When using this product

- avoid contact with the eyes.
- if contact occurs rinse thoroughly with water

Stop use and ask a doctor if

- irritation occurs or if there is no improvement within 4 weeks

Keep out of reach of children.

If swallowed, get medical help or contact a Poison Control Center right away

Directions

- shake well before using
- wash affected area and dry thoroughly
- apply a thin layer of the product over affected area (around the nails and underneath nail tips) twice daily or as directed by a doctor
- supervise children in the use of this product
- for athlete's foot, pay special attention to spaces between the toes; wear well-fitting, ventilated shoes and change shoes and socks at least once daily
- for athlete's foot and ringworm, use daily for 4 weeks. If condition persists longer, consult a doctor
- this product is not effective on the scalp or nails

Other information

- store at room temperature 15°-30°C (59°-86°F)

Inactive ingredients

Acetone, Aloe Barbadensis Leaf Powder, Propylene Glycol, Tocopherol (Vitamin E), Water

Questions or comments?

www.rooftopch.com
cservice@rooftopch.com